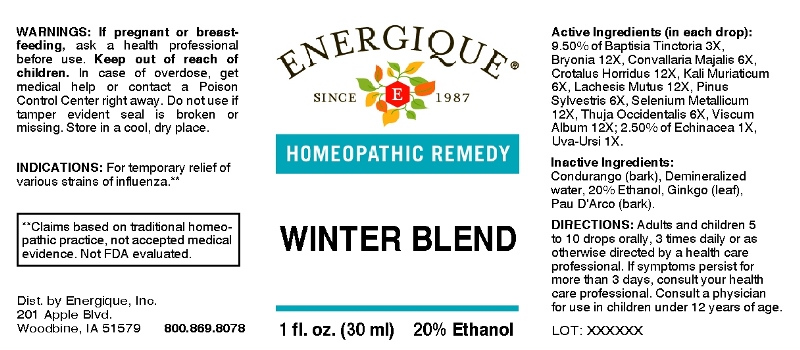 DRUG LABEL: WINTER BLEND
NDC: 44911-0109 | Form: LIQUID
Manufacturer: Energique, Inc.
Category: homeopathic | Type: HUMAN OTC DRUG LABEL
Date: 20240712

ACTIVE INGREDIENTS: ECHINACEA ANGUSTIFOLIA WHOLE 1 [hp_X]/1 mL; ARCTOSTAPHYLOS UVA-URSI LEAF 1 [hp_X]/1 mL; BAPTISIA TINCTORIA ROOT 3 [hp_X]/1 mL; CONVALLARIA MAJALIS 6 [hp_X]/1 mL; POTASSIUM CHLORIDE 6 [hp_X]/1 mL; PINUS SYLVESTRIS LEAFY TWIG 6 [hp_X]/1 mL; THUJA OCCIDENTALIS LEAFY TWIG 6 [hp_X]/1 mL; BRYONIA ALBA ROOT 12 [hp_X]/1 mL; CROTALUS HORRIDUS HORRIDUS VENOM 12 [hp_X]/1 mL; LACHESIS MUTA VENOM 12 [hp_X]/1 mL; SELENIUM 12 [hp_X]/1 mL; VISCUM ALBUM FRUITING TOP 12 [hp_X]/1 mL
INACTIVE INGREDIENTS: TABEBUIA IMPETIGINOSA BARK; MARSDENIA CONDURANGO BARK; GINKGO; WATER; ALCOHOL

DRUG FACTS:

ACTIVE INGREDIENTS:

(in each drop): 9.50% of Baptisia Tinctoria 3X, Bryonia 12X, Convallaria Majalis 6X, Crotalus Horridus 12X, Kali Muriaticum 6X, Lachesis Mutus 12X, Pinus Sylvestris 6X, Selenium Metallicum 12X, Thuja Occidentalis 6X, Viscum Album 12X; 2.50% of Echinacea 1X, Uva-Ursi 1X.

INDICATIONS:

For temporary relief of various strains of influenza.**

**Claims based on traditional homeopathic practice, not accepted medical evidence. Not FDA evaluated.

WARNINGS:

If pregnant or breast-feeding, ask a health professional before use.

Keep out of reach of children. In case of overdose, get medical help or contact a Poison Control Center right away.

Do not use if tamper evident seal is broken or missing.

Store in a cool, dry place.

KEEP OUT OF REACH OF CHILDREN:

In case of overdose, get medical help or contact a Poison Control Center right away.

DIRECTIONS:

Adults and children 5 to 10 drops orally, 3 times daily or as otherwise directed by a health care professional. If symptoms persist, consult your health care professional. Consult a physician for use in children under 12 years of age.

INDICATIONS:

For temporary relief of various strains of influenza.**

**Claims based on traditional homeopathic practice, not accepted medical evidence. Not FDA evaluated.

INACTIVE INGREDIENTS:

Condurango (bark), Demineralized water, 20% Ethanol, Ginkgo (leaf), Pau D'Arco (bark)

QUESTIONS:

Dist. by Energique, Inc.

201 Apple Blvd.

Woodbine, IA 51579 888.869.8078

PACKAGE LABEL DISPLAY:

ENERGIQUE
HOMEOPATHIC REMEDY
WINTER BLEND
1 fl oz. (30 ml)